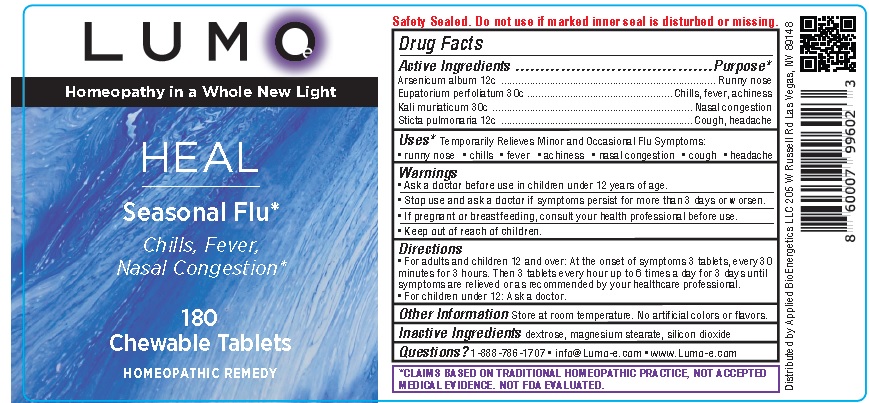 DRUG LABEL: LUMO Heal Seasonal Flu Companion
NDC: 81425-004 | Form: TABLET, CHEWABLE
Manufacturer: Applied Bioenergetics, LLC
Category: homeopathic | Type: HUMAN OTC DRUG LABEL
Date: 20251110

ACTIVE INGREDIENTS: ARSENIC TRIOXIDE 12 [hp_C]/1 1; EUPATORIUM PERFOLIATUM FLOWERING TOP 30 [hp_C]/1 1; POTASSIUM CHLORIDE 30 [hp_C]/1 1; LOBARIA PULMONARIA 12 [hp_C]/1 1
INACTIVE INGREDIENTS: DEXTROSE; MAGNESIUM STEARATE; SILICON DIOXIDE

LUMO-e Heal Seasonal Flu Companion

Drug Facts

Active Ingredients
Arsenicum album 12c
Eupatorium perfoliatum 30c
Kali muriaticum 30c
Sticta pulmonaria 12c

Purpose*
Arsenicum album ............................................................ Runny nose
Eupatorium perfoliatum ....................................Chills, fever, achiness
Kali muriaticum ....................................................... Nasal congestion
Sticta pulmonaria ................................................... Cough, headache

INDICATIONS AND USAGE

Uses* Temporarily Relieves Minor and Occasional Flu Symptoms:
• runny nose • chills • fever • achiness • nasal congestion • cough • headache

Warnings
• Ask a doctor before use in children under 12 years of age.
• Stop use and ask a doctor if symptoms persist for more than 3 days or worsen.
• If pregnant or breastfeeding, consult your health professional before use.

• Keep out of reach of children.

Directions
• For adults and children 12 and over: At the onset of symptoms 3 tablets, every 30
minutes for 3 hours. Then 3 tablets every hour up to 6 times a day for 3 days until
symptoms are relieved or as recommended by your healthcare professional.
• For children under 12: Ask a doctor.

Other Information Store at room temperature. No artificial colors or flavors.

Inactive Ingredients dextrose, magnesium stearate, silicon dioxide

QUESTIONS

Questions? 1-888-786-1707 • info@Lumo-e.com • www.Lumo-e.com

*CLAIMS BASED ON TRADITIONAL HOMEOPATHIC PRACTICE, NOT ACCEPTED
MEDICAL EVIDENCE. NOT FDA EVALUATED.

Product Label for LUMO-e HEAL

LUMO-e
Homeopathy in a Whole New Light

HEAL
Seasonal Flu*
Chills, Fever,
Nasal Congestion

180
Chewable Tablets

HOMEOPATHIC REMEDY

Safety Sealed. Do not use if marked inner seal is disturbed or missing.

*CLAIMS BASED ON TRADITIONAL HOMEOPATHIC PRACTICE, NOT ACCEPTED
MEDICAL EVIDENCE. NOT FDA EVALUATED.

Distributed by Applied BioEnergetics LLC 205 W Russell Rd Las Vegas, NV 89148

res